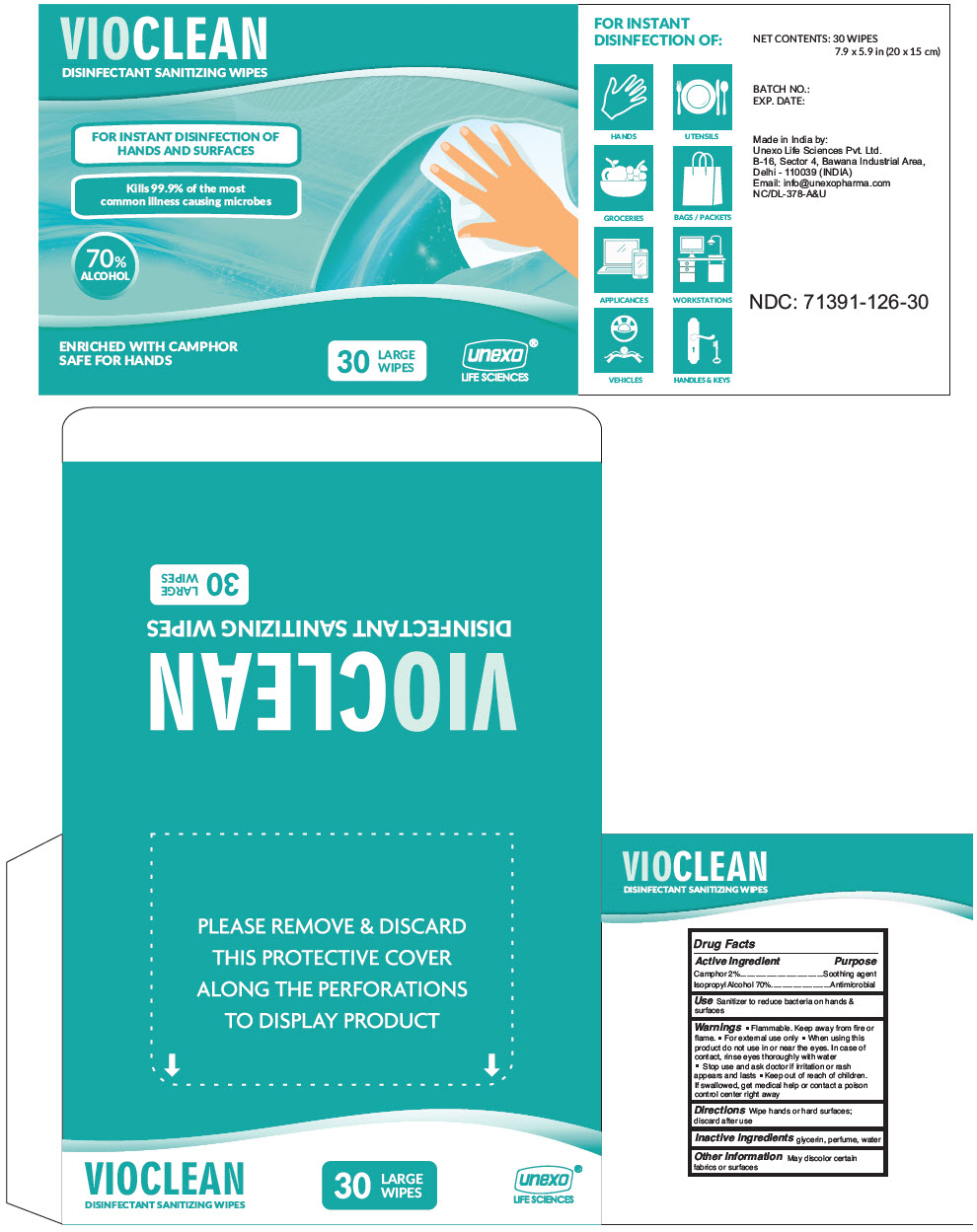 DRUG LABEL: Vioclean Disinfectant Wipes
NDC: 71391-126 | Form: PATCH
Manufacturer: Unexo Life Sciences, Private Limited
Category: otc | Type: HUMAN OTC DRUG LABEL
Date: 20200903

ACTIVE INGREDIENTS: Isopropyl Alcohol 3500 mg/1 1; Camphor (Synthetic) 100 mg/1 1
INACTIVE INGREDIENTS: Glycerin; Lemon Oil; Water

Vioclean Disinfectant Wipes

Drug Facts

ACTIVE INGREDIENT

Active Ingredient | Purpose
Camphor 2% | Soothing agent
Isopropyl Alcohol 70% | Antimicrobial

Use

Sanitizer to reduce bacteria on hands & surfaces

Warnings

- Flammable. Keep away from fire or flame.
- For external use only

- When using this product do not use in or near the eyes. In case of contact, rinse eyes thoroughly with water

- Stop use and ask doctor if irritation or rash appears and lasts

- Keep out of reach of children. If swallowed, get medical help or contact a poison control center right away

Directions

Wipe hands or hard surfaces; discard after use

Inactive ingredients

glycerin, perfume, water

Other Information

May discolor certain fabrics or surfaces

PRINCIPAL DISPLAY PANEL - 30 Wipe Pouch Box

VIOCLEAN
DISINFECTANT SANITIZING WIPES

FOR INSTANT DISINFECTION OF
HANDS AND SURFACES

Kills 99.9% of the most
common illness causing microbes

70%
ALCOHOL

ENRICHED WITH CAMPHOR
SAFE FOR HANDS

30
LARGE
WIPES

unexo®
LIFE SCIENCES